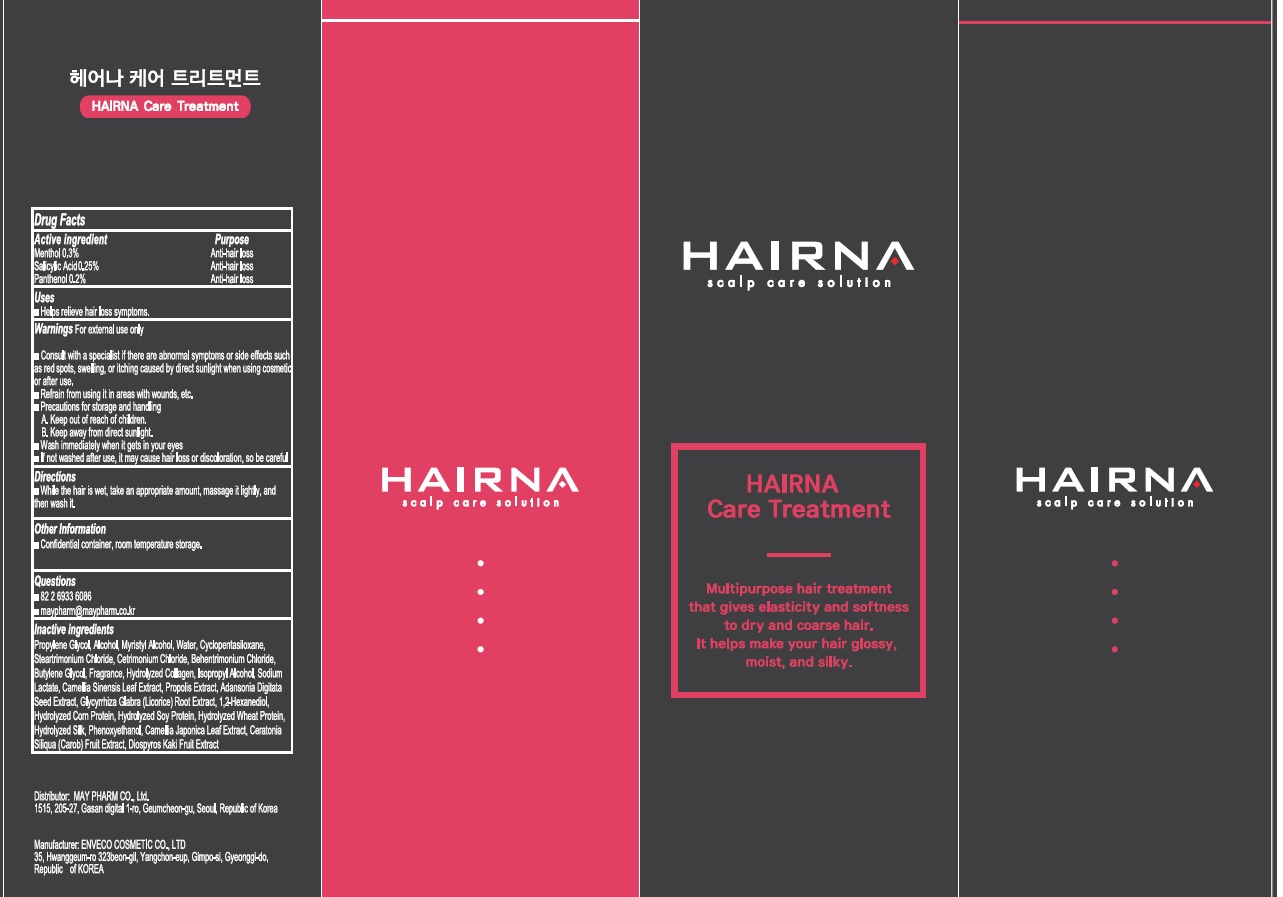 DRUG LABEL: HAIRNA Care Treatment
NDC: 82344-040 | Form: LIQUID
Manufacturer: MAYPHARM
Category: otc | Type: HUMAN OTC DRUG LABEL
Date: 20211129

ACTIVE INGREDIENTS: Menthol 0.3 g/100 mL; Salicylic Acid 0.25 g/100 mL; Panthenol 0.20 g/100 mL
INACTIVE INGREDIENTS: Propylene Glycol; Alcohol

ACTIVE INGREDIENTS

Menthol 0.3%
Salicylic Acid 0.25%
Panthenol 0.20%

PURPOSE

Anti-hair loss

Uses

■ Helps relieve hair loss symptoms.

WARNINGS

For external use only

■ Consult with a specialist if there are abnormal symptoms or side effects such as red spots, swelling, or itching caused by direct sunlight when using cosmetics or after use.
■ Refrain from using it in areas with wounds, etc.
■ Precautions for storage and handling
A. Keep out of reach of children.
B. Keep away from direct sunlight.
■ Wash immediately when it gets in your eyes
■ If not washed after use, it may cause hair loss or discoloration, so be careful

KEEP OUT OF REACH OF CHILDREN

Directions

■ Shake thoroughly before using, apply an appropriate amount on the scalp every day, and massage it with your fingers to get it absorbed.

Other Information

■ While the hair is wet, take an appropriate amount, massage it lightly, and then wash it.

Questions

■ 82 2 6933 6086
■ maypharm@maypharm.co.kr

INACTIVE INGREDIENTS

Propylene Glycol, Alcohol, Myristyl Alcohol, Water, Cyclopentasiloxane, Steartrimonium Chloride, Cetrimonium Chloride, Behentrimonium Chloride, Butylene Glycol, Fragrance, Hydrolyzed Collagen, Isopropyl Alcohol, Sodium Lactate, Camellia Sinensis Leaf Extract, Propolis Extract, Adansonia Digitata Seed Extract, Glycyrrhiza Glabra (Licorice) Root Extract, 1,2-Hexanediol, Hydrolyzed Corn Protein, Hydrolyzed Soy Protein, Hydrolyzed Wheat Protein, Hydrolyzed Silk, Phenoxyethanol, Camellia Japonica Leaf Extract, Ceratonia Siliqua (Carob) Fruit Extract, Diospyros Kaki Fruit Extract